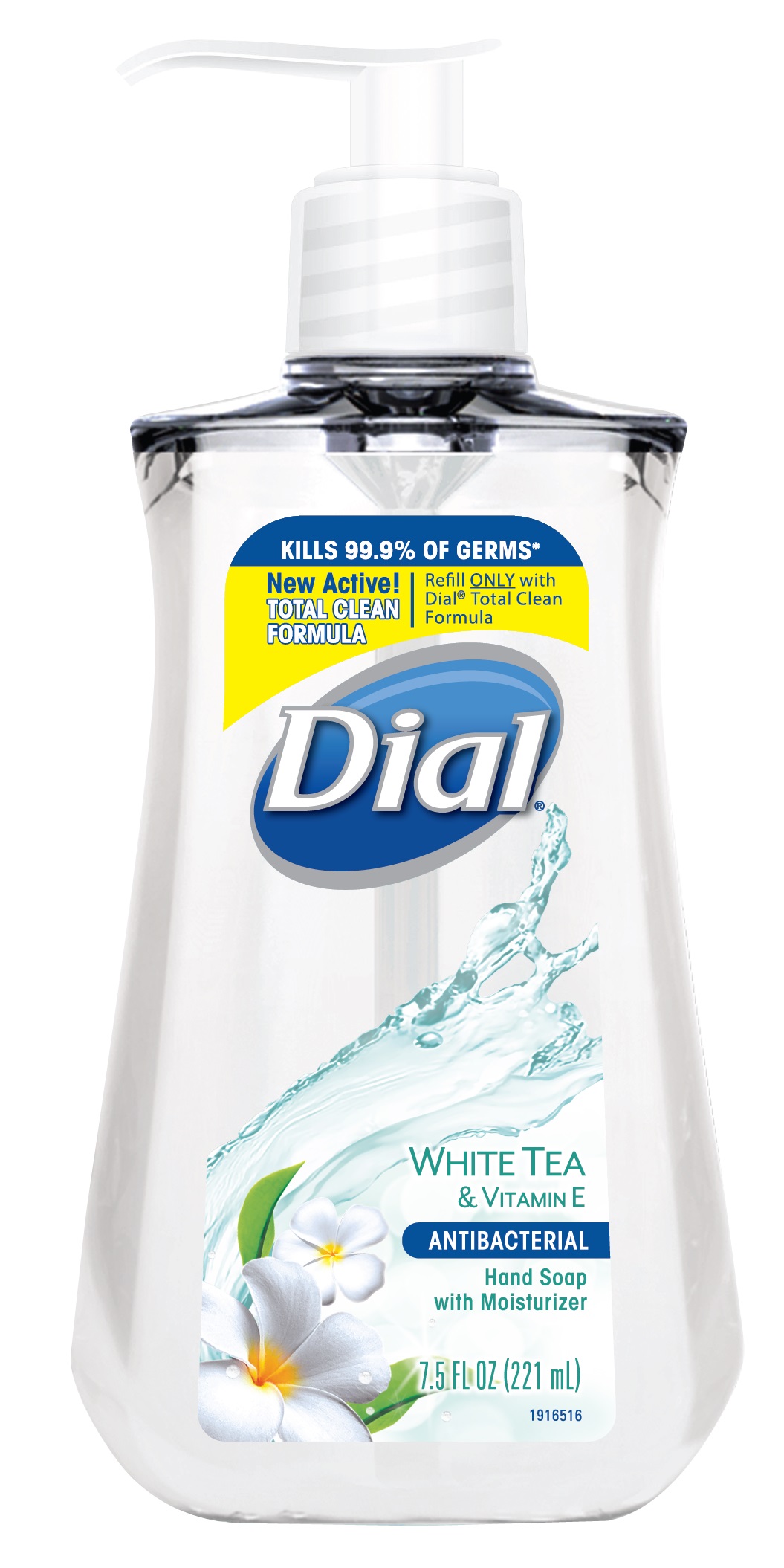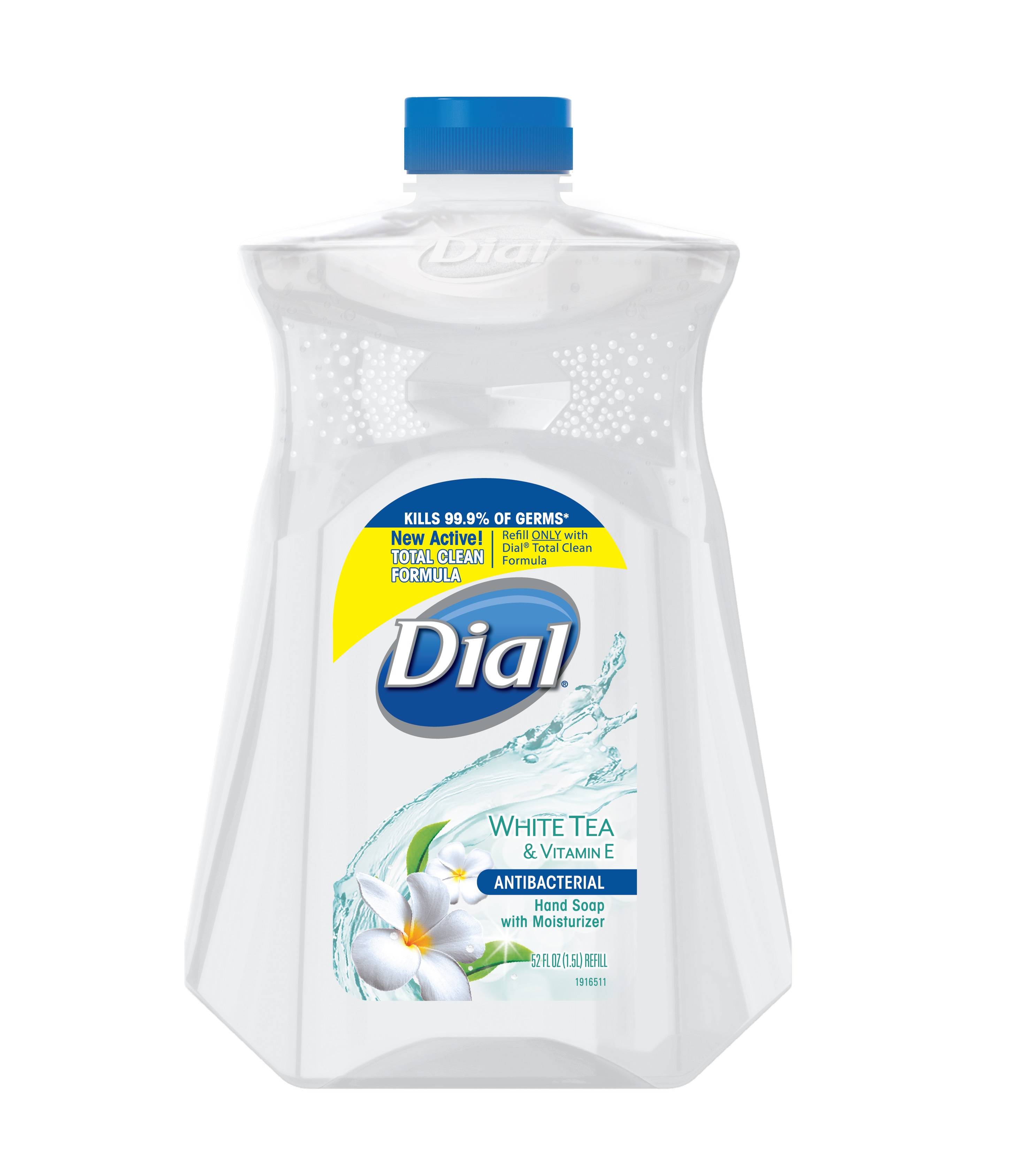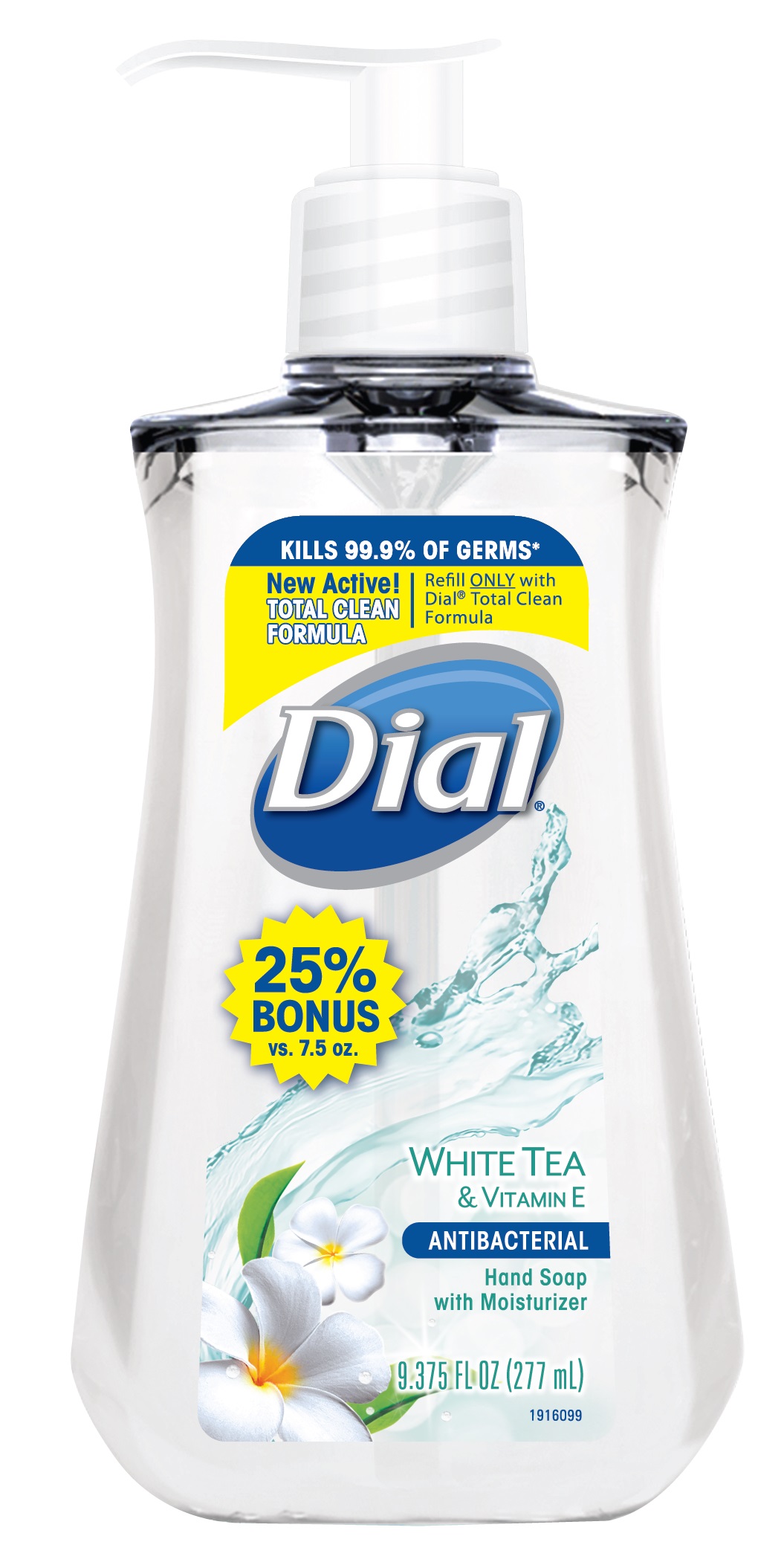 DRUG LABEL: Dial Antibacterial Hand Wash
NDC: 54340-245 | Form: SOLUTION
Manufacturer: The Dial Corporation, A Henkel Company
Category: otc | Type: HUMAN OTC DRUG LABEL
Date: 20141216

ACTIVE INGREDIENTS: Benzethonium Chloride .1 g/100 mL
INACTIVE INGREDIENTS: EDETATE SODIUM; Citric Acid Monohydrate; D&C RED NO. 33; Sodium Chloride; CETRIMONIUM CHLORIDE; Sodium Benzoate; FD&C BLUE NO. 1; .ALPHA.-TOCOPHEROL ACETATE; GREEN TEA LEAF; GLYCERIN; Lauramine Oxide; Lauramidopropylamine Oxide; COCO MONOETHANOLAMIDE; PEG-120 Methyl Glucose Dioleate

Dial White Tea And Vitamin E Antibacterial Hand Soap with Moisturizer

Drug Facts

Active Ingredient

Benzethonium Chloride 0.10%

PURPOSE

Antibacterial

PURPOSE

Uses - For handwashing to decrease bacteria on the skin

Warnings

For external use only

When using this product - Avoid contact with eyes. In case of eye contact, flush with water.

Stop use and ask a doctor if irritation and redness develops

Keep out of reach of children. If swallowed, get medical help or contact a Poison Control Center right away.

Directions

pump into hands, wet as needed

lather vigorously for at least 15 seconds

wash skin, rinse thoroughly and dry

INACTIVE INGREDIENT

Inactive Ingredients: Water, Centrimonium Chloride, Glycerin, Lauramine Oxide, Lauramidopropylamine Oxide, Sodium Chloride, Fragrance, Camellia Sinensis (White Tea) Leaf Extract, Tocopheryl Acetate, PEG-120 Methyl Glucose Dioleate, Cocamide MEA, Citric Acid, Sodium Benzoate, Tetrasodium EDTA, Blue 1, Red 33

* Encountered in household settings

Questions? 1-800-258-DIAL (3425)

Visit our website at www.dialsoap.com MADE IN USA

©2014 & Distributed by THE DIAL CORPORATION

a Henkel COMPANY SCOTTSDALE, AZ 85255

The distinctive design and elements of this package are propriatary and

owned by The dial Corporation, A Henkel Company

DOSAGE AND ADMINISTRATION

Topical Liquid

INDICATIONS AND USAGE

For handwashing to decrease bacteria on the skin

PACKAGE LABEL

Kills 99.9% of Germs*

New Active!

TOTAL CLEAN FORMULA

Refill ONLY with Dial© Total Clean Formula

DIAL

White Tea and Vitamin E Hand Soap with Moisturizer

Antibacterial

7.5 FL OZ (221 mL)